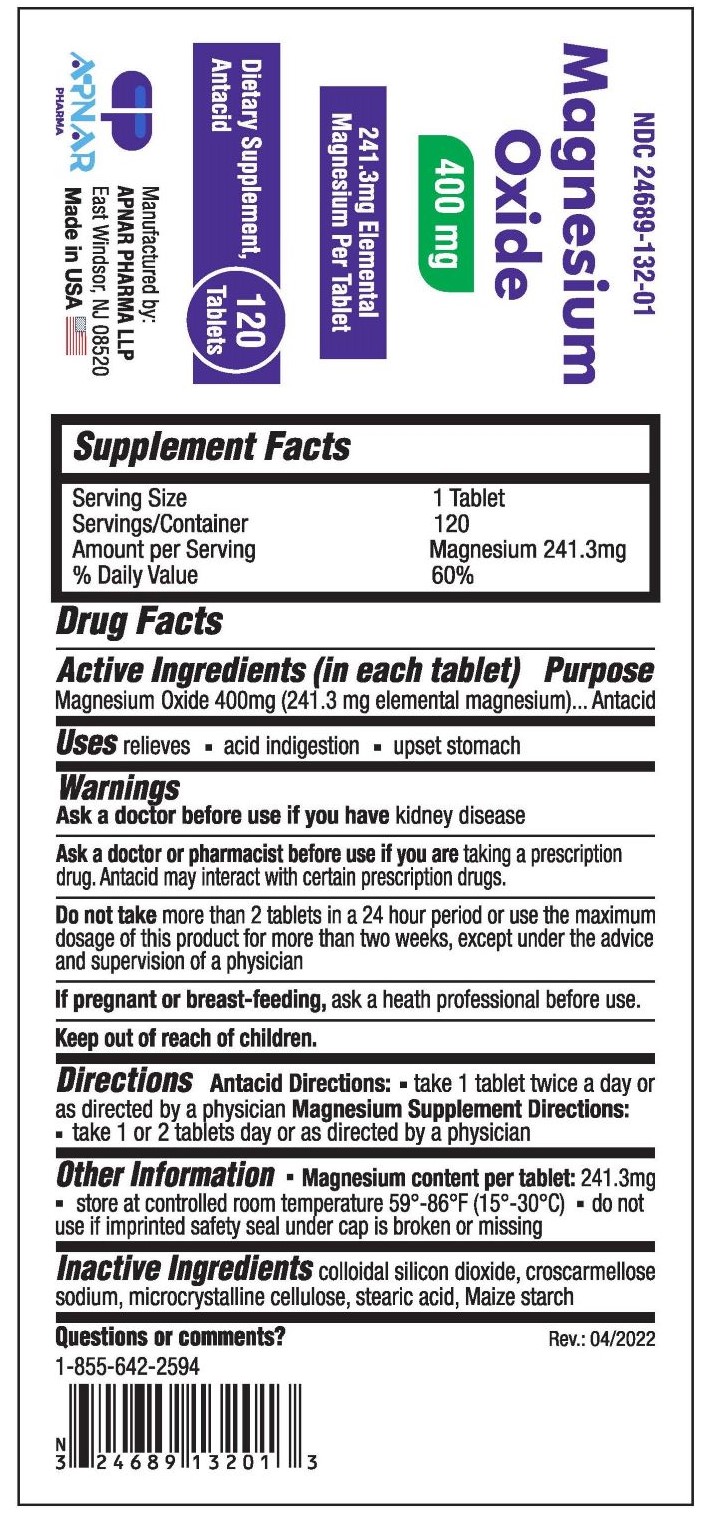 DRUG LABEL: Magnesium Oxide
NDC: 24689-132 | Form: TABLET
Manufacturer: APNAR PHARMA LP
Category: otc | Type: HUMAN OTC DRUG LABEL
Date: 20231021

ACTIVE INGREDIENTS: MAGNESIUM OXIDE 400 mg/1 1
INACTIVE INGREDIENTS: SILICON DIOXIDE; STEARIC ACID; CROSCARMELLOSE SODIUM; MICROCRYSTALLINE CELLULOSE; STARCH, CORN

Magnesium Oxide 400 mg Tablets

Active Ingredients (in each tablet)

Magnesium Oxide 400 mg (241.3 mg elemental magnesium)

Purpose

Antacid

Uses

relieves

- acid indigestion
- upset stomach

Warnings

Ask a doctor before use if you have kidney disease

Ask a doctor or pharmacist before use if you are taking a prescription drug. Antacid may interact with certain prescription drugs.

Do not take more than 2 tablets in a 24 hour period or use the maximum dosage of this product for more than two weeks, except under the advice and supervision of a physician

If pregnant or breast-feeding, ask a professional before use

Keep out of reach of children

Directions

Antacid Directions: take 1 tablet twice a day or as directed by a physician

Magnesium Supplement Directions: take 1 or 2 tablets day or as directed by a physician

Other information

- Magnesium content per tablet : 241.3 mg
- store at controlled room temperature 59°- 86°F (15°- 30°C)
- do not use if imprinted safety seal under cap is broken or missing

Inactive Ingredients

Colloidal silicon dioxide, croscarmellose sodium, microcrystalline cellulose, stearic acid, maize starch

Questions or comments?

1-855-642-2594

Rev.: 04/2022

Manufactured by:

APNAR PHARMA LLP

East Windsor, NJ 08520

Made in USA

PACKAGE LABEL

NDC 24689-132-01

Magnesium Oxide Tablets 400 mg

241.3 mg elemental Magnesium per tablet

Dietary supplement, Antacid

120 Tablets